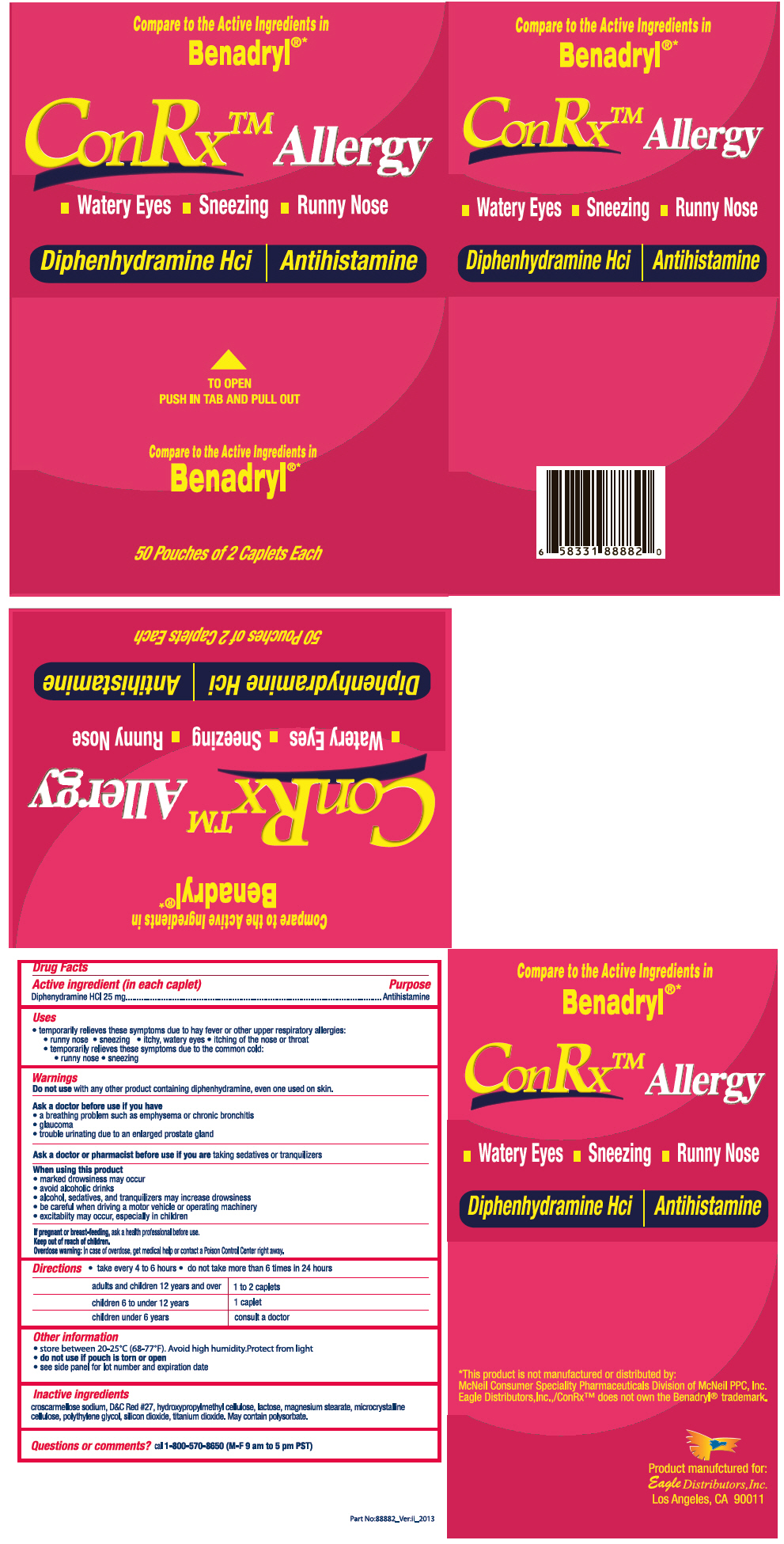 DRUG LABEL: ConRx Allergy
NDC: 68737-230 | Form: TABLET
Manufacturer: Eagle Distributors,Inc.
Category: otc | Type: HUMAN OTC DRUG LABEL
Date: 20130211

ACTIVE INGREDIENTS: Diphenhydramine Hydrochloride 25 mg/1 1
INACTIVE INGREDIENTS: CROSCARMELLOSE SODIUM; D&C RED NO. 27; HYPROMELLOSES; LACTOSE; MAGNESIUM STEARATE; CELLULOSE, MICROCRYSTALLINE; POLYETHYLENE GLYCOL 6000; SILICON DIOXIDE; TITANIUM DIOXIDE; POLYSORBATE 20

ConRx™ Allergy

Drug Facts

Active ingredient (in each caplet)

Diphenydramine HCl 25 mg

Purpose

Antihistamine

Uses

- temporarily relieves these symptoms due to hay fever or other upper respiratory allergies:
  - runny nose
  - sneezing
  - itchy, watery eyes
  - itching of the nose or throat
- temporarily relieves these symptoms due to the common cold:
  - runny nose
  - sneezing

Warnings

Do not use with any other product containing diphenhydramine, even one used on skin.

Ask a doctor before use if you have

- a breathing problem such as emphysema or chronic bronchitis
- glaucoma
- trouble urinating due to an enlarged prostate gland

Ask a doctor or pharmacist before use if you are taking sedatives or tranquilizers

When using this product

- marked drowsiness may occur
- avoid alcoholic drinks
- alcohol, sedatives, and tranquilizers may increase drowsiness
- be careful when driving a motor vehicle or operating machinery
- excitabiity may occur, especially in children

PREGNANCY OR BREAST FEEDING

If pregnant or breast-feeding, ask a health professional before use.

Keep out of reach of children.

Overdose warning

In case of overdose, get medical help or contact a Poison Control Center right away.

Directions

- take every 4 to 6 hours
- do not take more than 6 times in 24 hours

adults and children 12 years and over 1 to 2 caplets

children 6 to under 12 years 1 caplet,

children under 6 years consult a doctor

Other information

- store between 20-25°C (68-77°F). Avoid high humidity. Protect from light
- do not use if pouch is torn or open
- see side panel for lot number and expiration date

Inactive ingredients

croscarmellose sodium, D&C Red #27, hydroxypropylmethyl cellulose, lactose, magnesium stearate, microcrystalline cellulose, polythylene glycol, silicon dioxide, titanium dioxide. May contain polysorbate.

Questions or comments?

1-800-570-8650

PRINCIPAL DISPLAY PANEL - 50 Pouch Box

Compare to the Active Ingredients in

Benadryl®*

ConRx™ Allergy

■ Watery Eyes ■ Sneezing ■ Runny Nose

Diphenhydramine Hci | Antihistamine

TO OPEN
PUSH IN TAB AND PULL OUT

Compare to the Active Ingredients in
Benadryl®*

50 Pouches of 2 Caplets Each